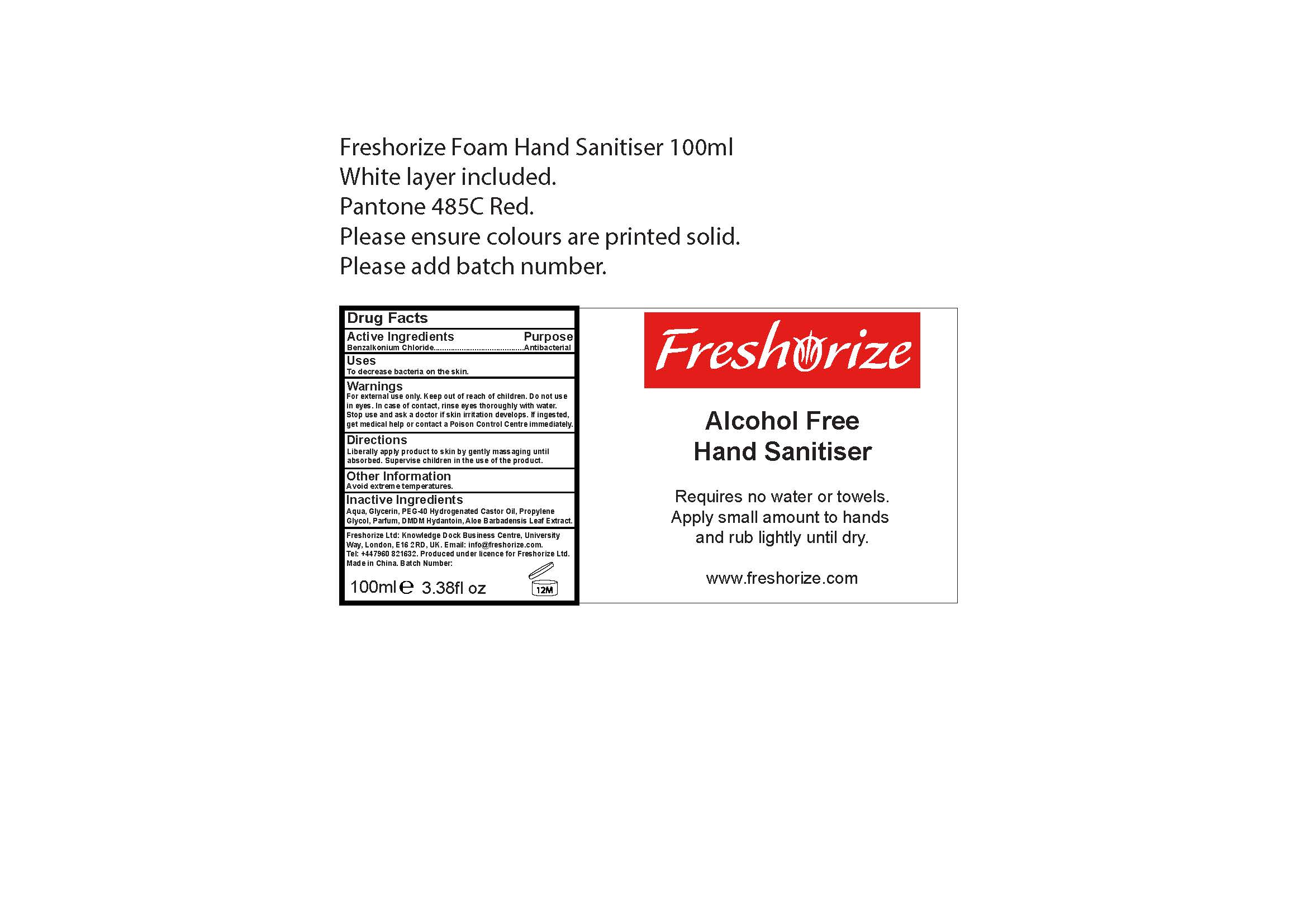 DRUG LABEL: Freshorize Alcohol Free Foaming Hand Sanitizer
NDC: 52305-600 | Form: LOTION
Manufacturer: Freshorize Ltd
Category: otc | Type: HUMAN OTC DRUG LABEL
Date: 20200615

ACTIVE INGREDIENTS: BENZALKONIUM CHLORIDE 0.13 g/100 mL
INACTIVE INGREDIENTS: HYDROGENATED CASTOR OIL 0.75 g/100 mL; DMDM HYDANTOIN 0.2 g/100 mL; GLYCERIN 3 g/100 mL; WATER 95.07 g/100 mL; ALOE VERA LEAF 0.1 g/100 mL

Alcohol Free Foam Hand Sanitizer

Uses:

To decrease bacteria on the skin.

Warnings

For external use only.

Do not use in eyes. In case of contact, rinse eyes thoroughly with water.
Stop use and ask a doctor is skin irritation develops.

If ingested, get medical help or contact a Poison Control Center immediately.

Warnings:

Keep out of reach of children.

Directions:

Liberally apply product to sin by gently massaging until absorbed.
Supervise children in the use of this product.

Other Information:

Avoid extreme temperatures.

Inactive Ingredients:

Water (Aqua), PEG-40 Hydrogenated Castor Oil, Parfum, Aloe Barbadensis Leaf Extract

Drug Facts

Active Ingredients
Benzalkonium Chloride

Purpose

Antibacterial.

Product / Brand Name Label

Freshorize Alcohol Free Hand Sanitizer

Requires no water or towels.
Apply small amounts to hands and rub lightly until dry.

www.freshorize.com